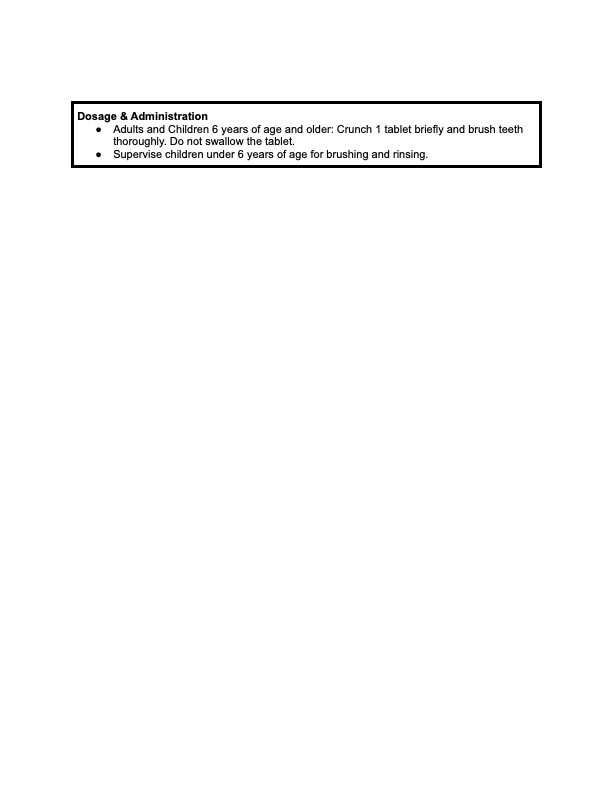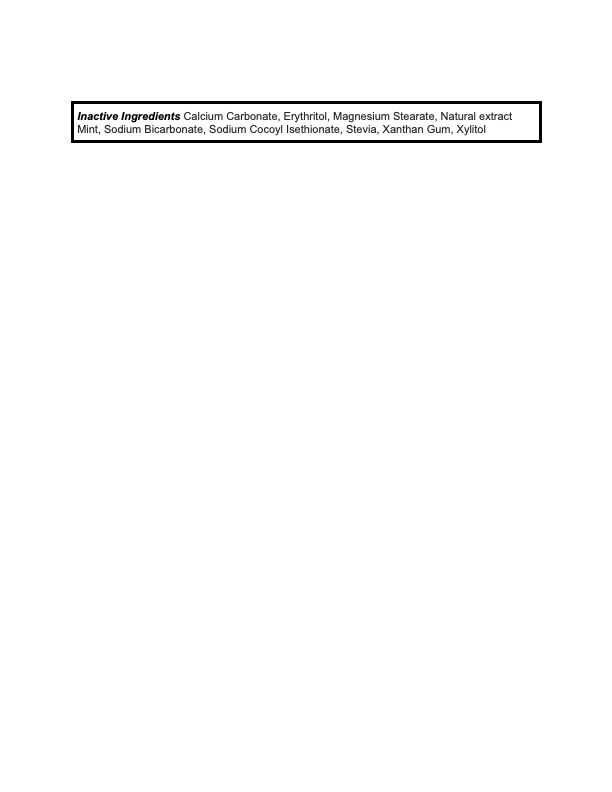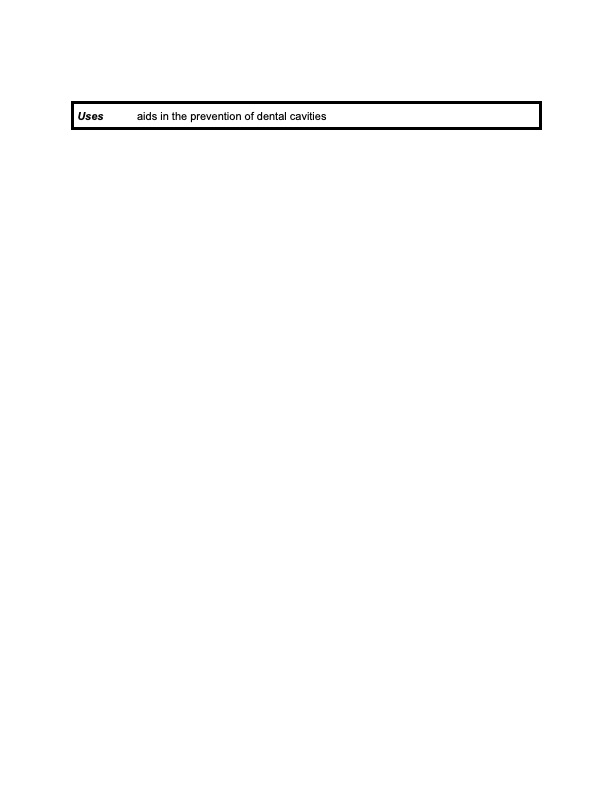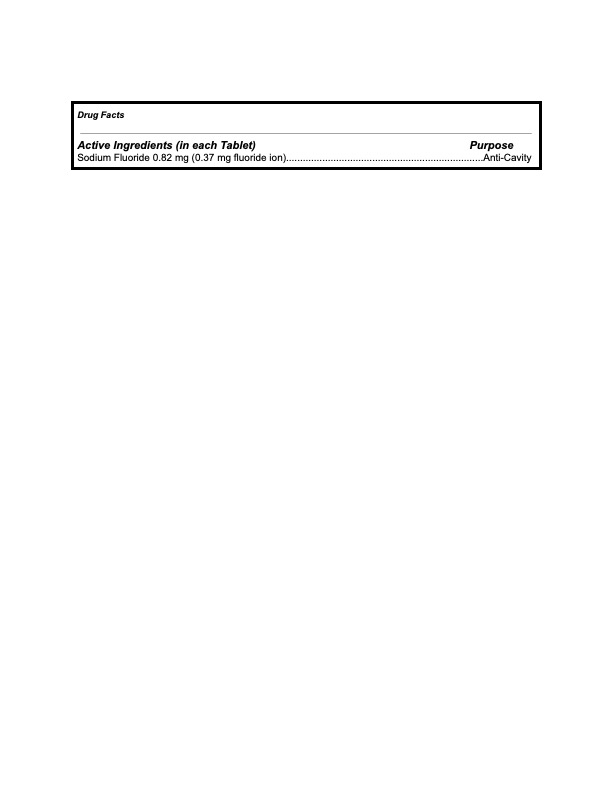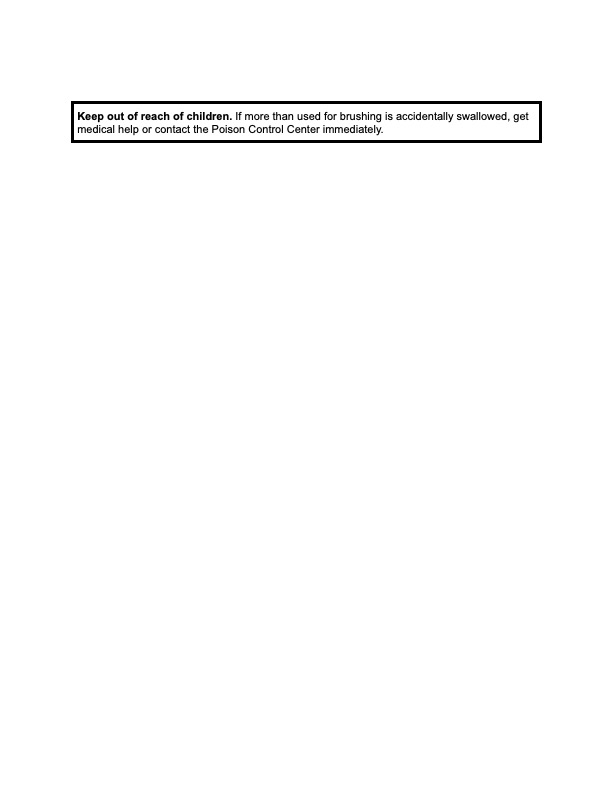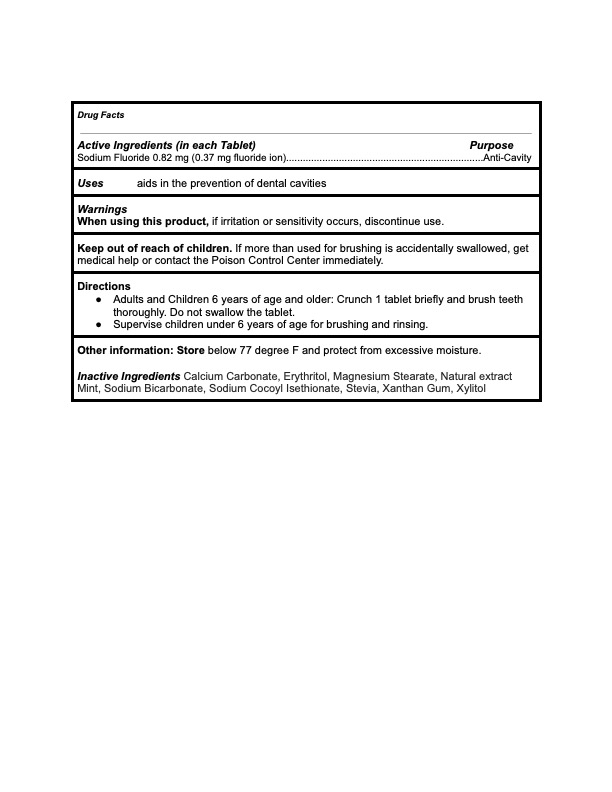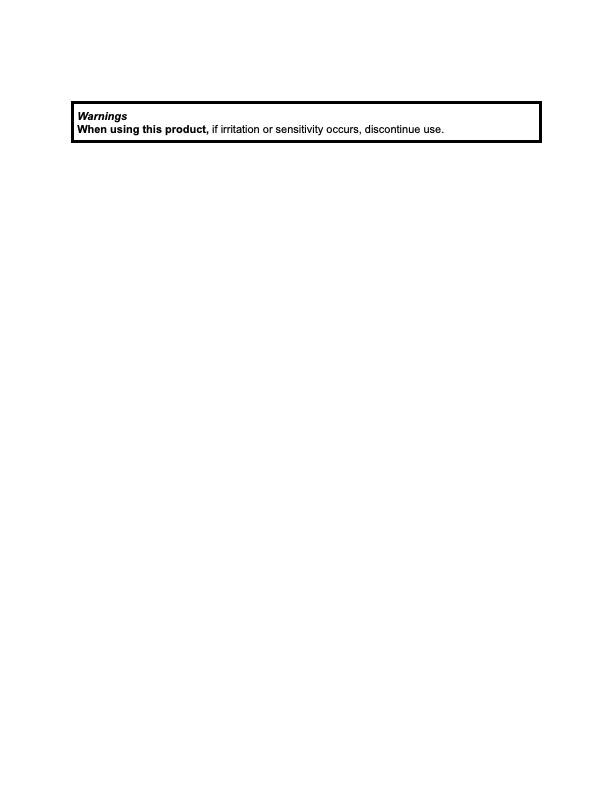 DRUG LABEL: KAYLAAN
NDC: 82091-115 | Form: TABLET, CHEWABLE
Manufacturer: Kaylaan LLC
Category: otc | Type: HUMAN OTC DRUG LABEL
Date: 20250109

ACTIVE INGREDIENTS: SODIUM FLUORIDE 0.37 mg/440 mg
INACTIVE INGREDIENTS: XANTHAN GUM; STEVIA LEAF; MINT; MAGNESIUM STEARATE; ERYTHRITOL; XYLITOL; SODIUM COCOYL ISETHIONATE; CINNAMON; CALCIUM CARBONATE; SODIUM BICARBONATE

Kaylaan Cinnamon Toothpaste Tablet Refill